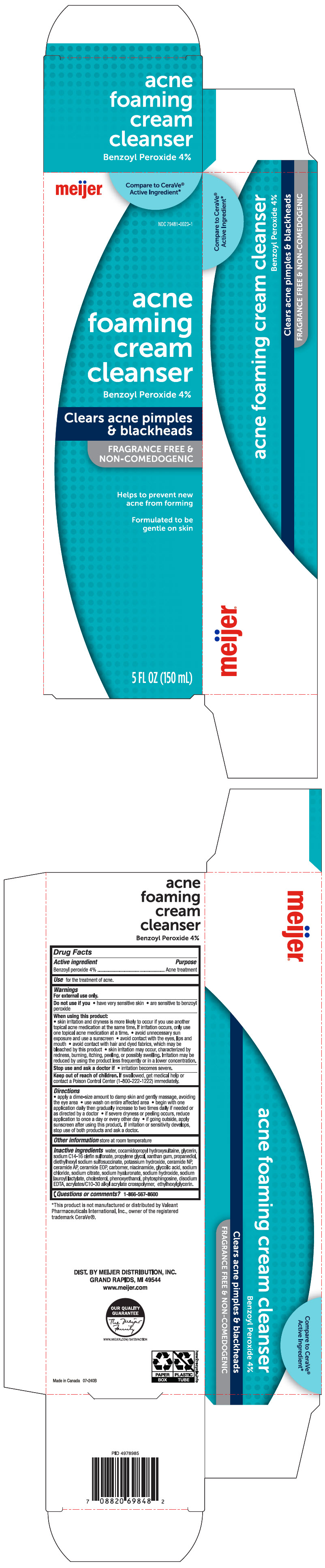 DRUG LABEL: Meijer Acne Foaming Cleanser
NDC: 79481-0023 | Form: CREAM
Manufacturer: Meijer Distribution, Inc
Category: otc | Type: HUMAN OTC DRUG LABEL
Date: 20241115

ACTIVE INGREDIENTS: Benzoyl Peroxide 40 mg/1 mL
INACTIVE INGREDIENTS: Water; Cocamidopropyl Hydroxysultaine; Glycerin; Sodium C14-16 Olefin Sulfonate; Propylene Glycol; Xanthan Gum; Propanediol; DOCUSATE SODIUM; Potassium Hydroxide; Ceramide NP; Ceramide AP; CERAMIDE 1; CARBOMER HOMOPOLYMER, UNSPECIFIED TYPE; Niacinamide; GLYCOLIC ACID; Sodium Chloride; SODIUM CITRATE, UNSPECIFIED FORM; HYALURONATE SODIUM; Sodium Hydroxide; Sodium Lauroyl Lactylate; Cholesterol; Phenoxyethanol; Phytosphingosine; EDETATE DISODIUM; CARBOMER INTERPOLYMER TYPE A (ALLYL SUCROSE CROSSLINKED); Ethylhexylglycerin

Meijer® Acne Foaming Cream Cleanser
Acne Treatment

Drug Facts

Active ingredient

Benzoyl peroxide 4%

Purpose

Acne Treatment

Use

for the treatment of acne.

Warnings

For external use only.

Do not use if you

- have very sensitive skin
- are sensitive to benzoyl peroxide

When using this product

- skin irritation and dryness is more likely to occur if you use another topical medication at the same time. If irritation occurs, only use one topical acne medication at a time
- avoid unnecessary sun exposure and use a sunscreen
- avoid contact with eyes, lips and mouth
- avoid contact with hair or dyed fabrics, which may be bleached by this product
- skin irritation may occur, characterized by redness, burning, itching, peeling, or possibly swelling. Irritation may be reduced by using the product less frequently or in a lower concentration.

Stop use and ask a doctor

- if skin irritation becomes severe.

Keep out of reach of children. If swallowed, get medical help or contact a Poison Control Center (1-800-222-122) immediately.

Directions

- apply a dime-size amount to damp skin and gently massage, avoiding the eye area.
- use wash on entire affected area
- begin with one application daily, then gradually increase to two to three times daily if needed or as directed by a doctor
- if severe dryness or peeling occurs, reduce application to once a day or every other day
- if going outside, apply sunscreen after using this product. If irritation or sensitivity develops, stop use of both products and ask a doctor.

Other information

store at room temperature

Inactive ingredients

water, cocamidopropyl hydroxysultaine, glycerin, sodium C14-16 olefin sulfonate, propylene glycol, xanthan gum, propanediol, diethylhexyl sodium sulfosuccinate, potassium hydroxide, ceramide NP, ceramide AP, ceramide EOP, carbomer, niacinamide, glycolic acid, sodium chloride, sodium citrate, sodium hyaluronate, sodium hydroxide, sodium lauroyl lactylate, cholesterol, phenoxyethanol, phytosphingosine, disodium EDTA, acrylates C10-30 alkyl acrylate crosspolymer, ethylhexylglycerin.

Questions or comments?

1-866-567-8600

DIST. BY MEIJER DISTRIBUTION, INC.
GRAND RAPIDS, MI 49544

PRINCIPAL DISPLAY PANEL - 150 mL Tube Carton

meijer®

Compare to CeraVe®
Active Ingredient*

NDC 79481-0023-1

acne
foaming
cream
cleanser

Benzoyl Peroxide 4%

Clears acne pimples
& blackheads

FRAGRANCE FREE &
NON-COMEDOGENIC

Helps to prevent new
acne from forming

Formulated to be
gentle on skin

5 FL OZ (150 mL)